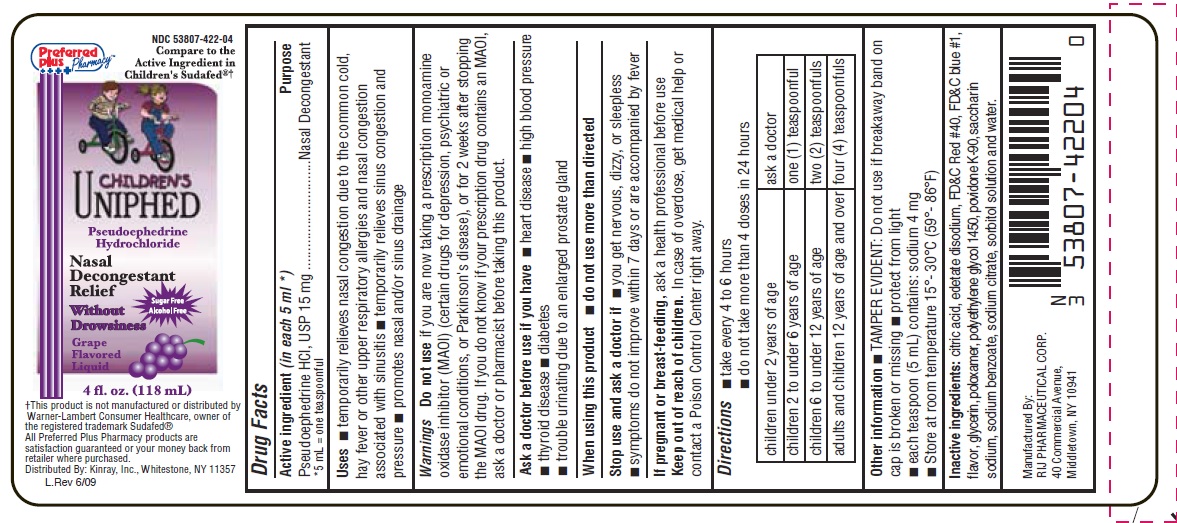 DRUG LABEL: Childrens Uniphed 
NDC: 53807-422 | Form: LIQUID
Manufacturer: Rij Pharmaceutical Corporation
Category: otc | Type: HUMAN OTC DRUG LABEL
Date: 20180430

ACTIVE INGREDIENTS: Pseudoephedrine hydrochloride 15 mg/5 mL
INACTIVE INGREDIENTS: anhydrous citric acid; edetate disodium; FD&C blue no. 1; FD&C red no. 40; glycerin; poloxamer 407; polyethylene glycols; povidone K90; water; saccharin sodium; sodium benzoate; sodium citrate; sorbitol

Drug Facts

Drug Facts

Active ingredient (in each 5 mL* [* 5 mL = one teaspoonful])

Pseudoephedrine HCl, USP 15 mg

Purpose

Nasal Decongestant

Uses

- temporarily relieves nasal congestion due to the common cold, hay fever or other upper respiratory allergies and nasal congestion associated with sinusitis
- temporarily relieves sinus congestion and pressure
- promotes nasal and/or sinus drainage

Warnings

Do not use if you are now taking a prescription monoamine oxidase inhibitor (MAOI) (certain drugs for depression, psychiatric or emotional conditions, or Parkinson's disease), or for 2 weeks after stopping the MAOI drug. If you do not know if your prescription drug contains an MAOI, ask a doctor or pharmacist before giving this product.

Ask a doctor before use if you have

- heart disease
- high blood pressure
- thyroid disease
- diabetes
- trouble urinating due to an enlarged prostate gland

When using this product do not use more than directed

Stop use and ask a doctor if

- you get nervous, dizzy, or sleepness
- symptoms do not improve within 7 days or are accompanied by fever

If pregnant or breast-feeding,

ask a health professional before use

Keep out of reach of children. In case of overdose, get medical help or contact a Poison Control Center right away

Directions

- take every 4 to 6 hours
- do not take more than 4 doses in 24 hours

children under 2 years of age | ask a doctor
children 2 to under 6 years of age | one (1) teaspoonful
children 6 to under 12 years of age | two (2) teaspoonfuls
adults and children 12 years of age and over | four (4) teaspoonfuls

Other information

- TAMPER EVIDENT: Do not use if breakaway band on cap is broken or missing
- protect from light
- each teaspoon (5 mL) contains: sodium 4 mg
- Store at room temperature 15º - 30ºC (59º - 86ºF)

Inactive ingredients

citric acid, edetate disodium, FD&C Red #40, FD&C blue #1, flavor, glycerin, poloxamer, polyethylene glycol, povidone K-90, saccharin sodium, sodium benzoate, sodium citrate, sorbitol solution, and water